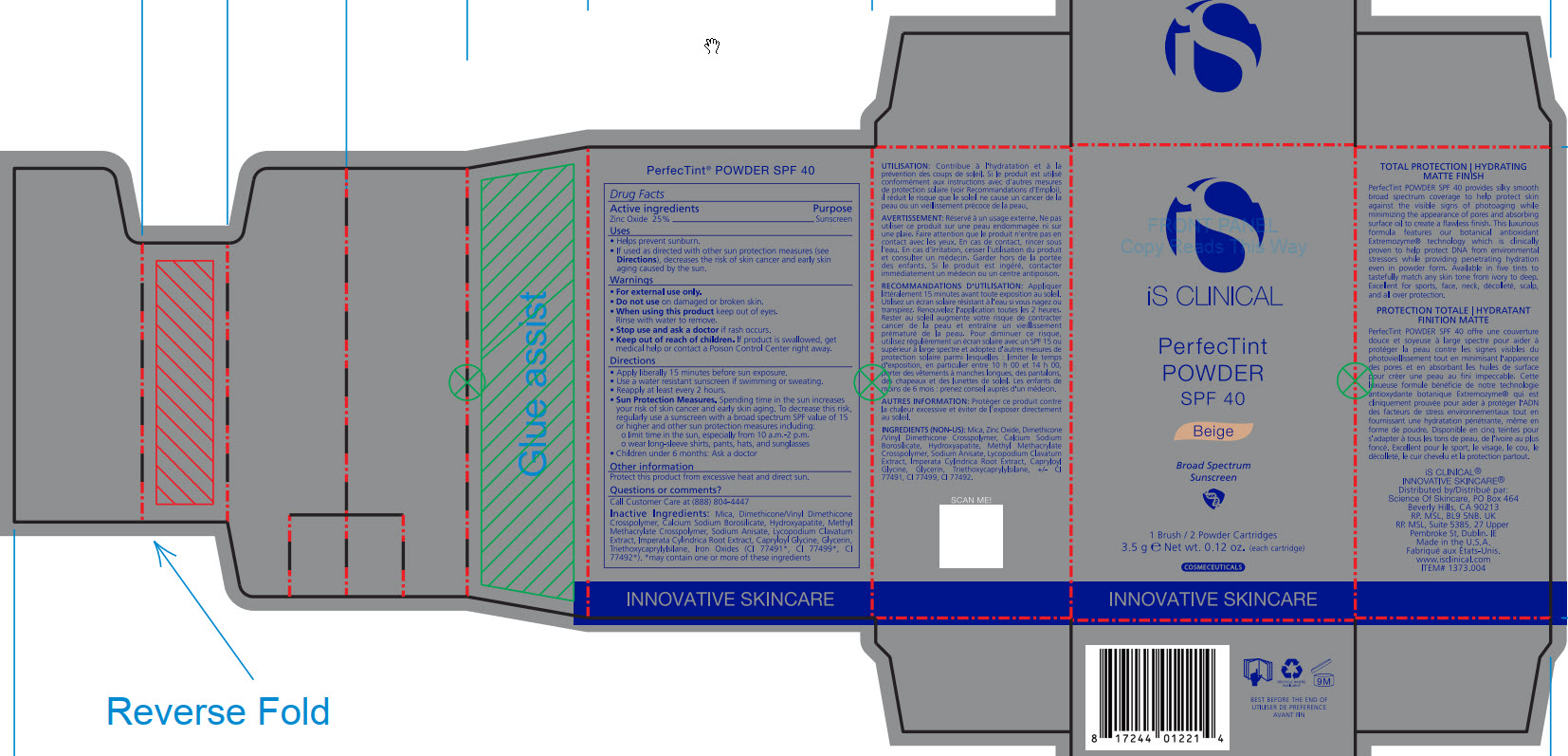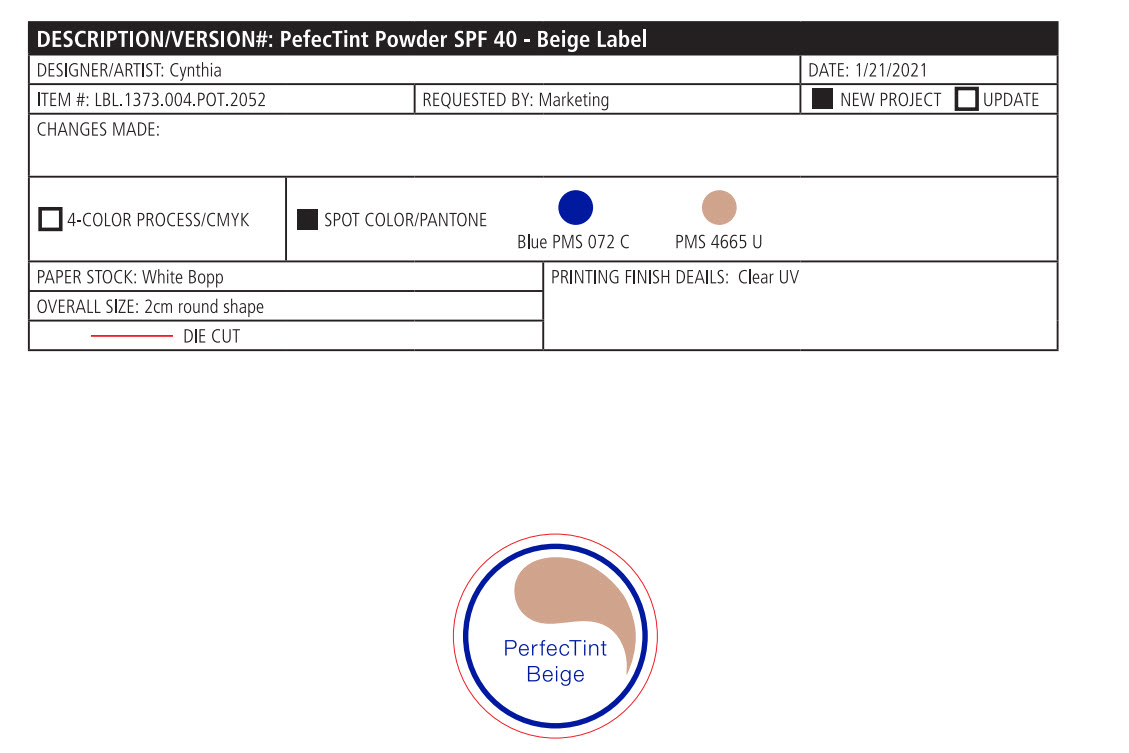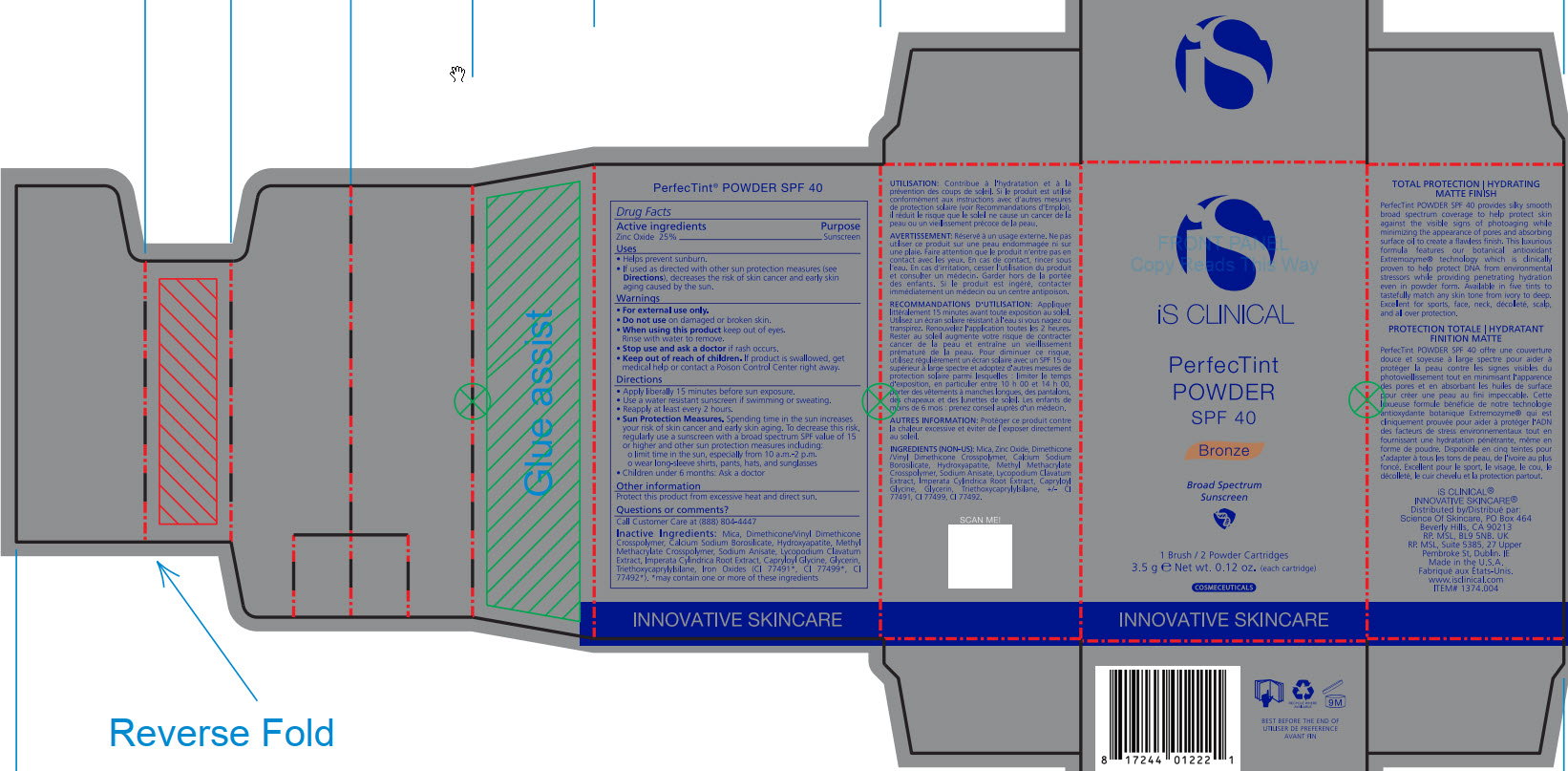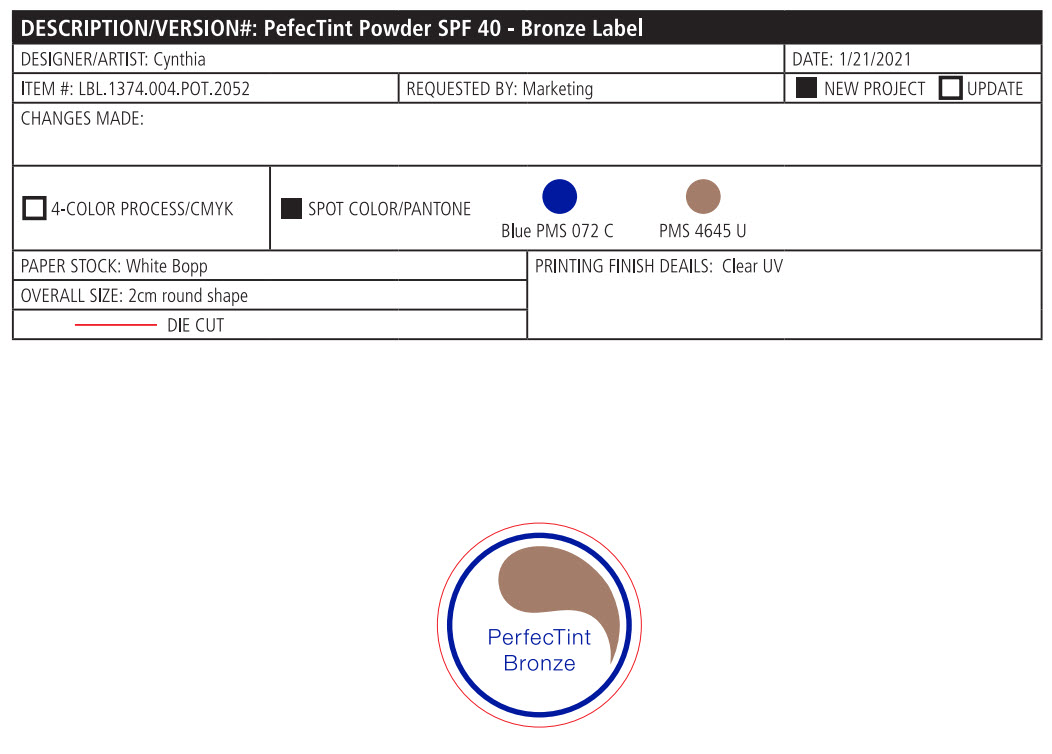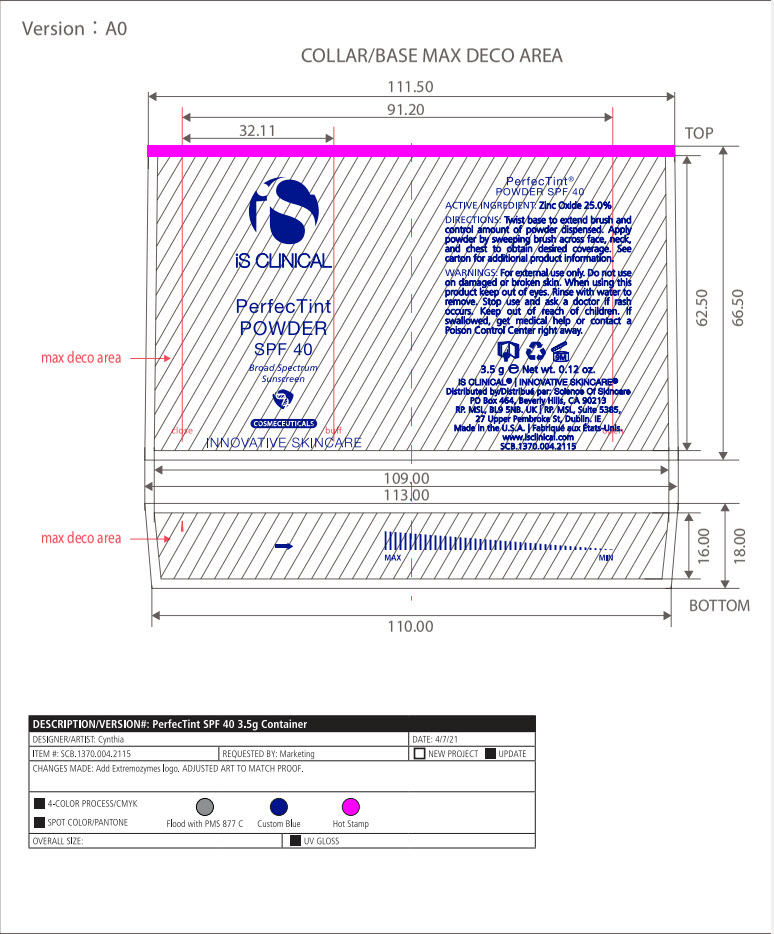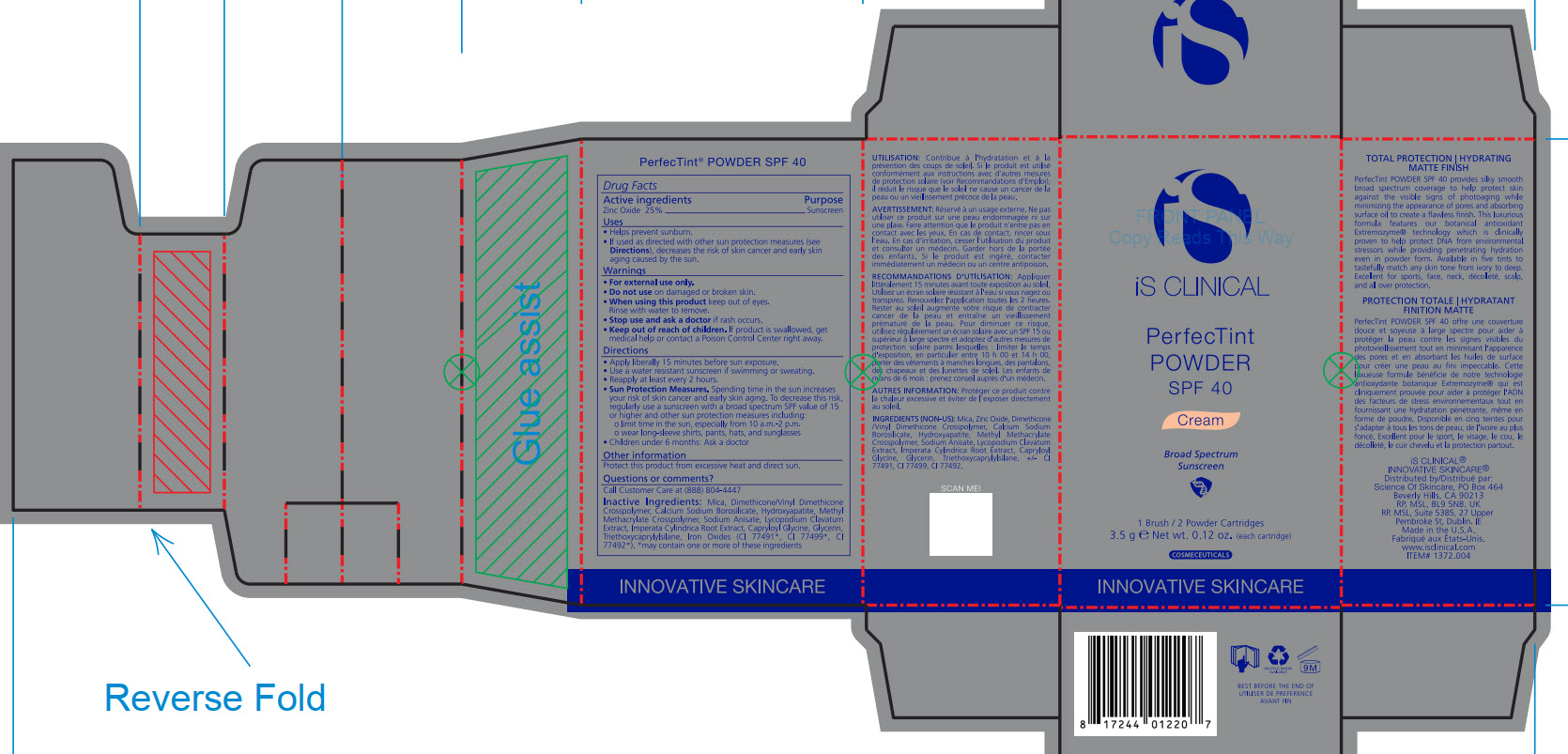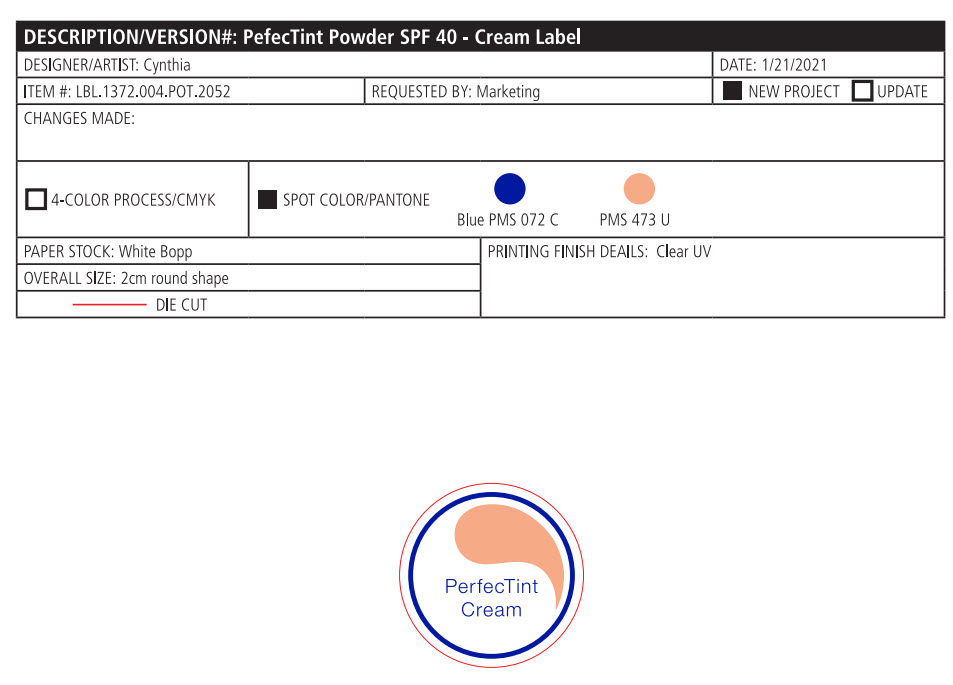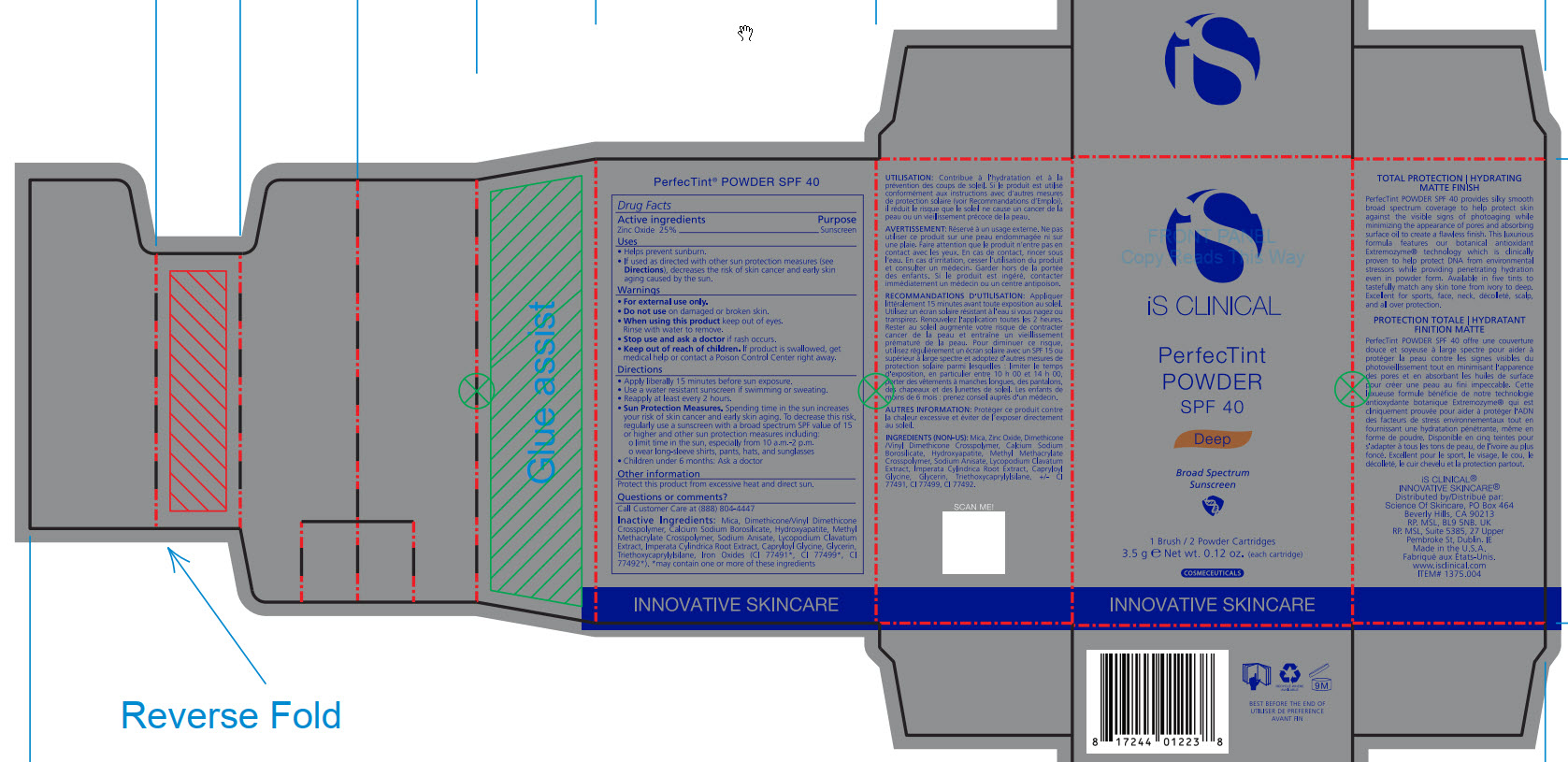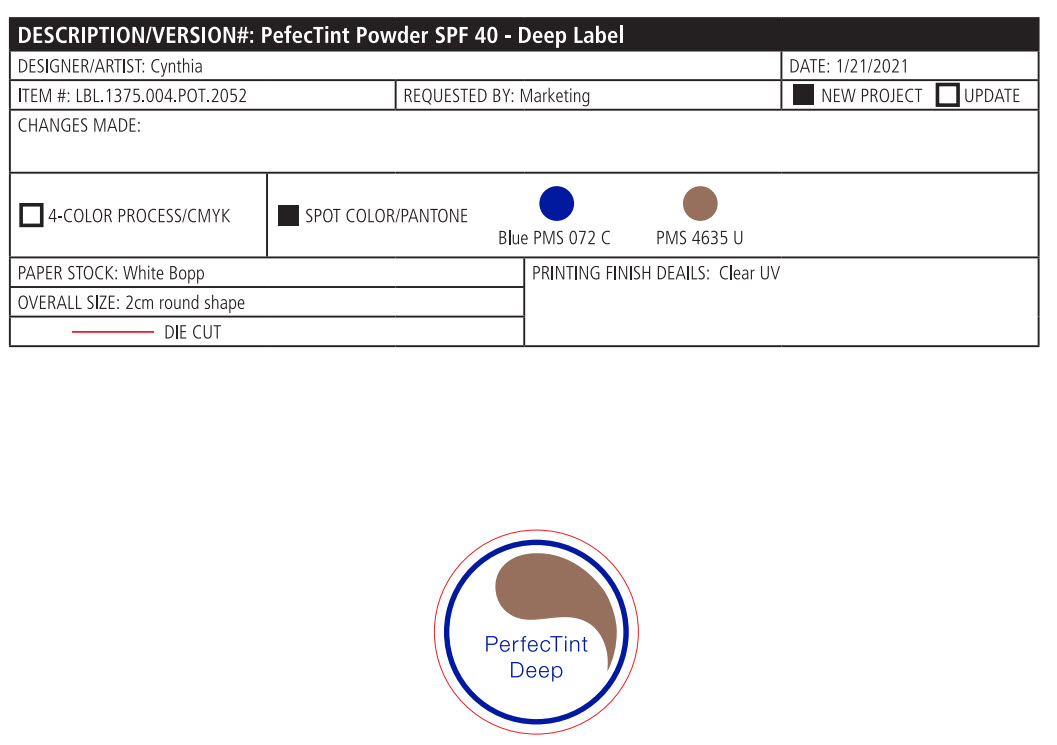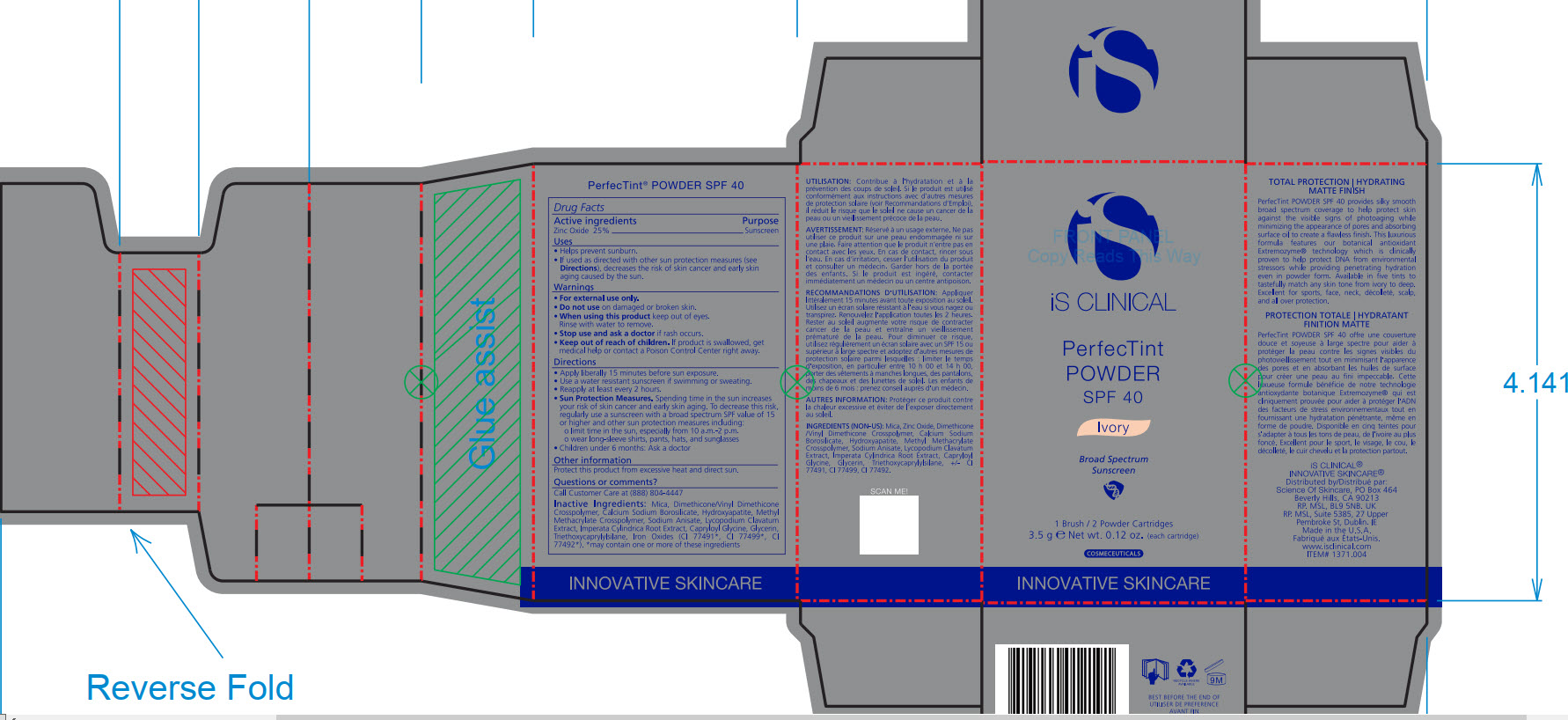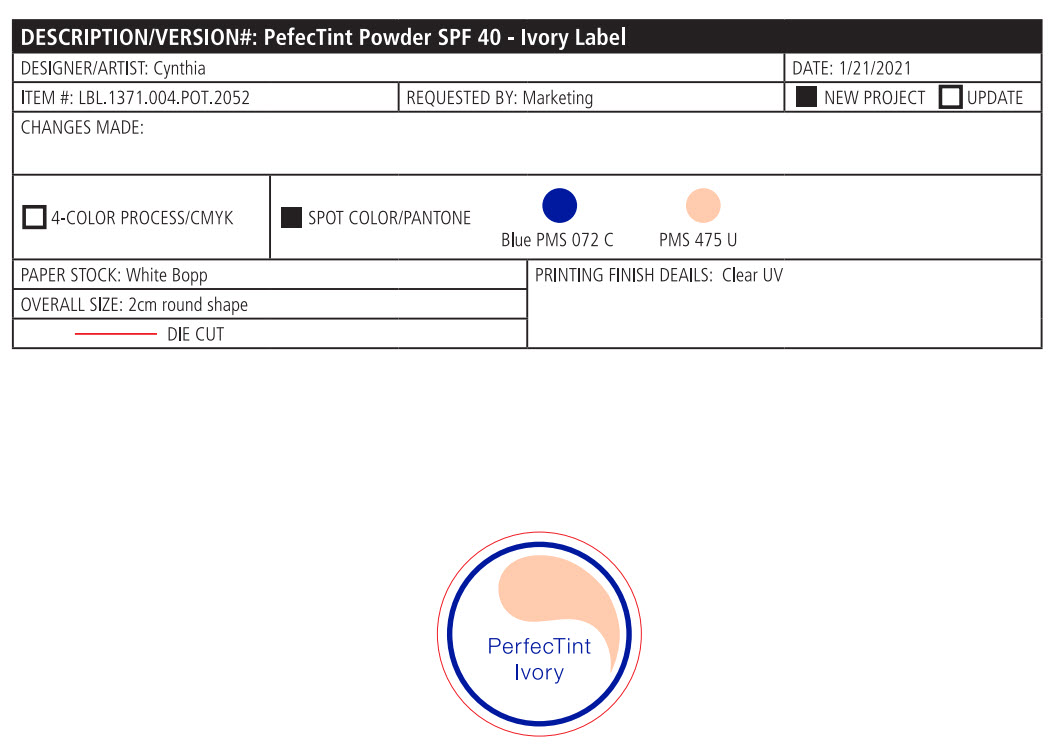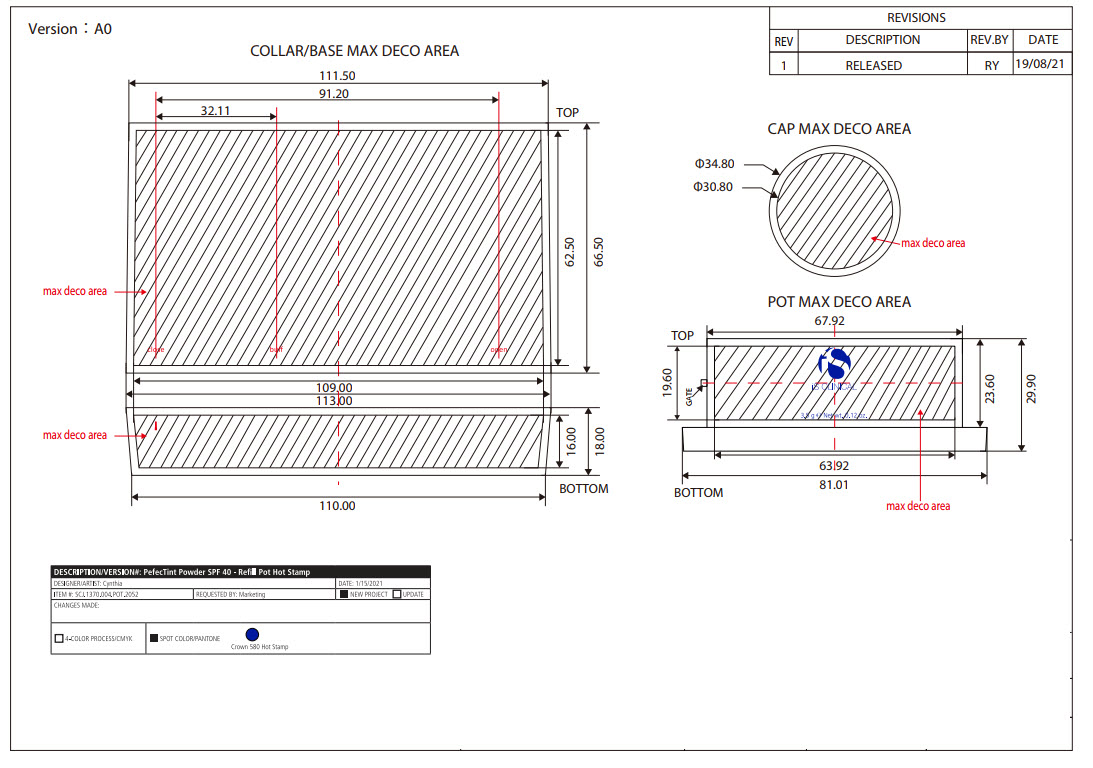 DRUG LABEL: PerfecTint Powder SPF 40
NDC: 69219-111 | Form: POWDER
Manufacturer: Science of Skincare
Category: otc | Type: HUMAN OTC DRUG LABEL
Date: 20250109

ACTIVE INGREDIENTS: ZINC OXIDE 25 g/100 g
INACTIVE INGREDIENTS: FERRIC OXIDE YELLOW; TRIETHOXYCAPRYLYLSILANE; MICA; CALCIUM ALUMINUM BOROSILICATE; SODIUM ANISATE; LYCOPODIUM CLAVATUM WHOLE; CAPRYLOYL GLYCINE; TRIBASIC CALCIUM PHOSPHATE; IMPERATA CYLINDRICA ROOT; GLYCERIN; FERROSOFERRIC OXIDE; DIMETHICONE/VINYL DIMETHICONE CROSSPOLYMER (SOFT PARTICLE); METHYL METHACRYLATE/GLYCOL DIMETHACRYLATE CROSSPOLYMER; FERRIC OXIDE RED

PerfecTint Powder SPF 40 (69219-111)

ACTIVE INGREDIENT

Zinc Oxide 25%

PURPOSE

Sunscreen

INDICATIONS AND USAGE

Apply liberally 15 minutes before sun exposure

WARNINGS

For external use only

Do not use on damaged or broken skin

When using this product keep out of eyes.

Rinse with water to remove.

Stop use and ask a doctor if rash occurs

Keep out of reach of children. If product is swallowed, get medical help or contact a Poison Control Center right away

DOSAGE AND ADMINISTRATION

Apply liberally 15 minutes before sun exposure.

Use a water-resistant sunscreen if swimming or sweating.

Reapply at least every 2 hours.

Sun Protection Measures. Spending time in the sun increase your risk of skin cancer and early skin aging. To decrease this risk, regularly use a sunscreen with a broad spectrum SPF value of 15 or higher and other sun protection measures including:

limit time in the sun, especially from 10am - 2pm.

wear long-sleeve shirts, pants, hats, and sunglasses

Children under 6 months: Ask a doctor

OTHER SAFETY INFORMATION

Protect this product from excessive heat and direct sun.

QUESTIONS

Call Customer Care at (888)-804-4447

INACTIVE INGREDIENT

Mica, Dimethicone/Vinyl Dimethicone Crosspolymer, Calcium Sodium Borosilicate, Hydroxyapatite, Methyl Methacrylate Crosspolymer, Sodium Anisate, Lycopodium Clavatum Extract, Imperata Cylindrica Root Extract, Capryloyl Glycine, Glycerin, Triethoxycaprylylsiliane, Ironxe Oxides(CI 77491*, CI 77499*, CI77492*). *may contain one or more of these ingredients